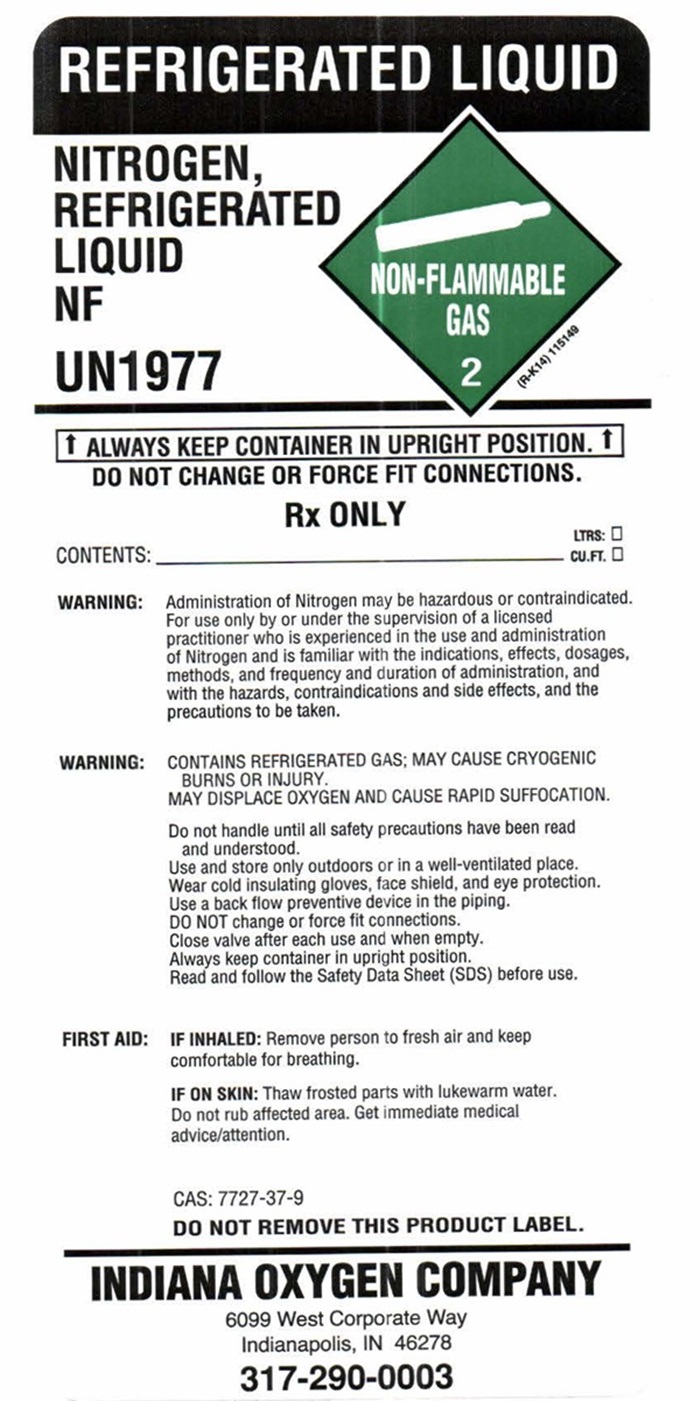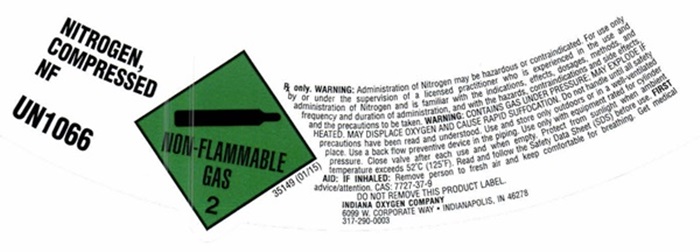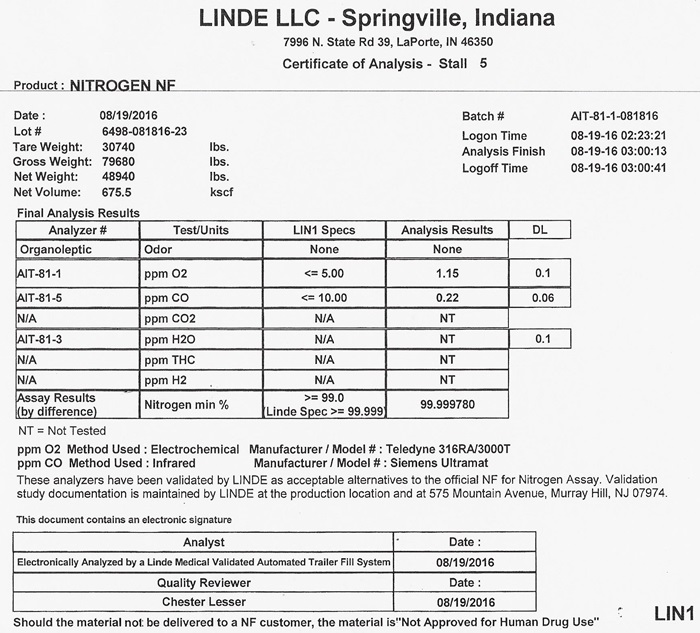 DRUG LABEL: NITROGEN
NDC: 48546-0003 | Form: GAS
Manufacturer: Indiana Oxygen Company Inc
Category: prescription | Type: HUMAN PRESCRIPTION DRUG LABEL
Date: 20241023

ACTIVE INGREDIENTS: NITROGEN 99 L/100 L

Nitrogen

NITROGEN COMPRESSED LABEL

NITROGEN, COMPRESSED NF UN1066

NON-FLAMMABLE GAS 2 35149 (01/15)

Rx only. WARNING: Administration of Nitrogen may be hazardous or contraindicated. For use only by or under the supervision of a licensed practioner who is experienced in the use and administration of Nitrogen and is familiar with the indications, effects, dosages, methods, and frequency and duration of administration, and with the hazards, contraindications and side effects and the precautions to be taken. WARNING: CONTAINS GAS UNDER PRESSURE; MAY EXPLODE, IF HEATED, MAY DISPLACE OXYGEN AND CAUSE RAPID SUFFOCCATION. Do not handle until all safety precautions have been read and understood. Use and store only outdoors or in a well-ventilated place. Use a back flow preventive device in the piping. Use only with equipment rated for cylinder pressure. Close valve after each use and when empty. Protect from sunlight when ambient temperature exceeds 52°C (125°F). Read and follow the Safety Data Sheet (SDS) before use. FIRST AID; IF INHALED; Remove person to fresh air and keep comfortable for breathing. Get medical advice/attention. CAS: 7727-37-9 DO NOT REMOVE THIS PRODUCT LABEL

INDIANA OXYGEN COMPANY

6099 WEST CORPORATE WAY • INDIANAPOLIS, IN 46278

317-290-0003

NITROGEN REFRIGERATED LIQUID LABEL

REFRIGERATED LIQUID

NITROGEN, REFRIGERATED LIQUID NF UN1977

NON-FLAMMABLE GAS 2 (R-K14) 115149

↑ALWAYS KEEP CONTAINER IN UPRIGHT POSITION.↑

DO NOT CHANGE OR FORCE FIT CONNECTIONS.

RX ONLY

CONTENTS: ___________________________________ LTRS: ___ CU FT: ___

WARNING: Administration of Nitrogen may be hazardous or contraindicated. For use only by or under the supervision of a licensed practitioner who is experienced in the use and administration of Nitrogen and is familiar with the indications, effects, dosages, methods, and frequency and duration of administration, and with the hazards, contraindications and side effects and the precautions to be taken.

WARNING: CONTAINS REFRIGERATED GAS; MAY CAUSE CRYOGENIC BURNS OR INJURY. MAY DISPLACE OXYGEN AND CAUSE RAPID SUFFOCATION.

Do not handle until all safety precautions have been read and understood.

Use and store only outdoors or in a well-ventilated place. Wear cold insulating gloves, face shield, and eye protection. Use a back-flow preventive device in the piping. DO NOT change or force fit connections.

Close valve after each use and when empty.

Always keep container in upright position.

Read and follow the Safety Data Sheet (SDS) before use.

FIRST AID: IF INHALED: Remove person to fresh air and keep comfortable for breathing.

IF ON SKING: Thaw frosted parts with lukewarm water. Do not rub affected area. Get immediate medical advice/attention.

CAS: 7727-37-9

DO NOT REMOVE THIS PRODUCT LABEL.

INDIANA OXYGEN COMPANY

6099 West Corporate Way

Indianapolis, IN 46278

317-290-0003

NITROGEN CERTIFICATE OF ANALYSIS

Certificate of Analysis - Nitrogen NF Customer ________________________ Vendor / Supplier _____________________________ This letter is to provide you with the certification you requested for Nitrogen NF, Lot number ___________. supplied to you in cylinders / vessels by our location. These cylinders were filled in accordance with the standard operating procedures utilized for the manufacture of Medical Gases. By following these procedures, our location ensures that products are safely manufactured in compliance with FDA's Current Good Manufacturing Regulations. CAUTION: Vendor supplies this certification to customer to assist customer in ensuring compliance with 21 CFR 211.84. This certification does not eliminate customer's obligation to cmply with other portions of 21 CFR 210 and 211 including but not limited to 21 CFR 211.165 (finished product testing) for cylinders and vessels filled from these supply cylinders. These cylinders are not certified for instrument calibration purposes.

TEST/REQUIREMENT NF SPECIFICATION LOT ANALYSIS
IDENTIFICATION PASS
ODOR NO APPRECIABLE ODOR
OXYGEN LESS THAN 1.0%
CARBON MONOXIDE LESS THAN 10 PPM
ASSAY GREATER THAN 99.0%

THE METHODOLOGY BEING USED TO PERFORM THE NF TEST FOR ASSAY IS INDICATED BELOW:

________________________ PARAMAGNETIC ANALYZER MODEL NUMBER ___________________

________________________ ELECTROCHEMICAL ANALYZER MODEL NUMBER ______________

_______________________ GAS CHROMATOGRAPHY OFFICIAL USP / NF METHOD

SUPPLIER SIGNATURE ___________________ DATE _________________

J 700 a1 (01/03) BR COMPLIANCE ASSOCIATES LLC